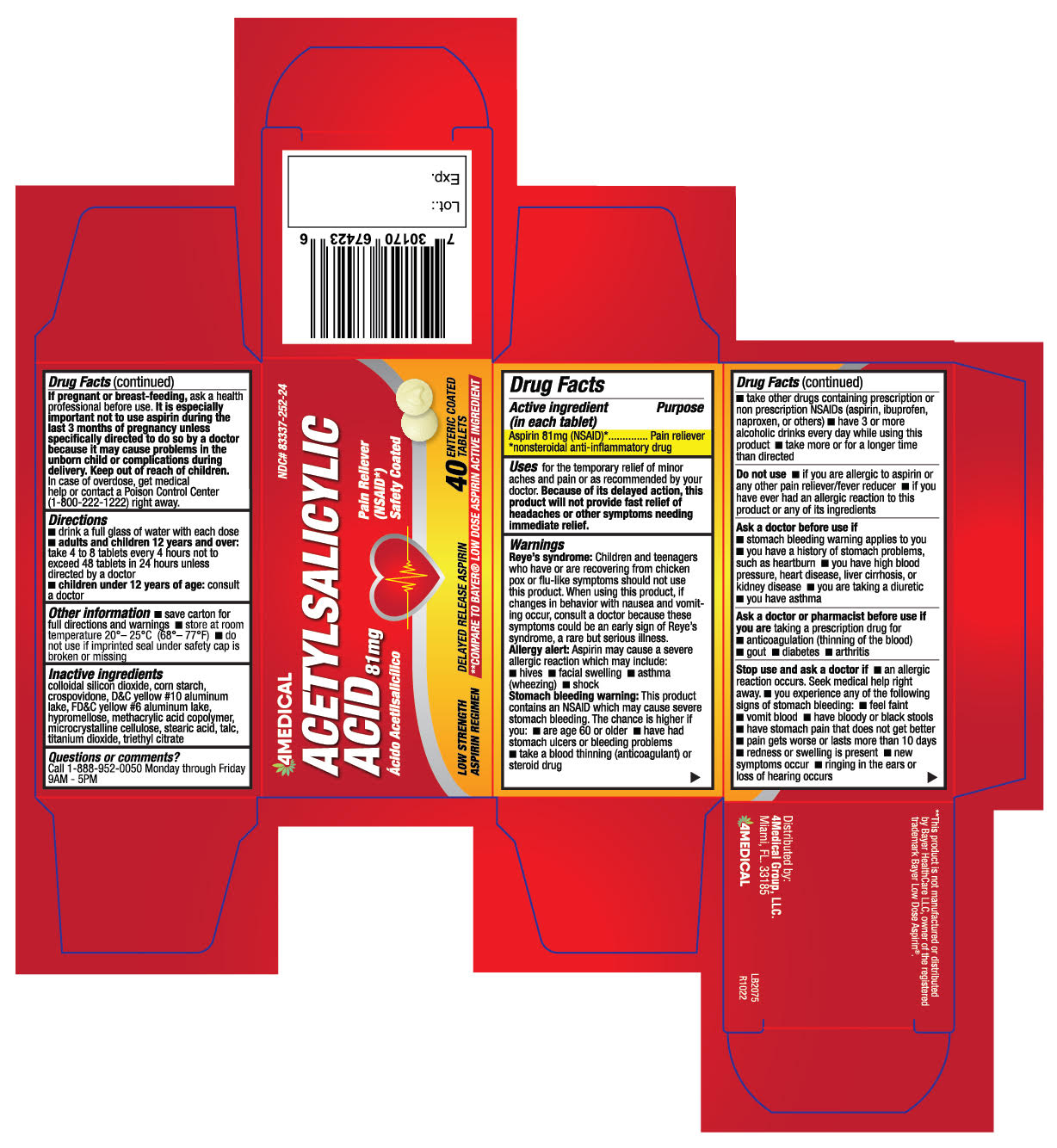 DRUG LABEL: Acetylsalicylic Acid
NDC: 83337-252 | Form: TABLET
Manufacturer: 4Medical Group, LLC
Category: otc | Type: HUMAN OTC DRUG LABEL
Date: 20250115

ACTIVE INGREDIENTS: ASPIRIN 81 mg/1 1
INACTIVE INGREDIENTS: STEARIC ACID; TALC; TRIETHYL CITRATE; CROSPOVIDONE; METHACRYLIC ACID; MICROCRYSTALLINE CELLULOSE; TITANIUM DIOXIDE; FD&C YELLOW NO. 6; HYPROMELLOSE, UNSPECIFIED; SILICON DIOXIDE; D&C YELLOW NO. 10; STARCH, CORN

4Medical Acetylsalicylic Acid 81mg - NDC: 83337-252-24

Box Acetylsalicylic Acid - 4MedicalGroup. PC 252 - SPC 372